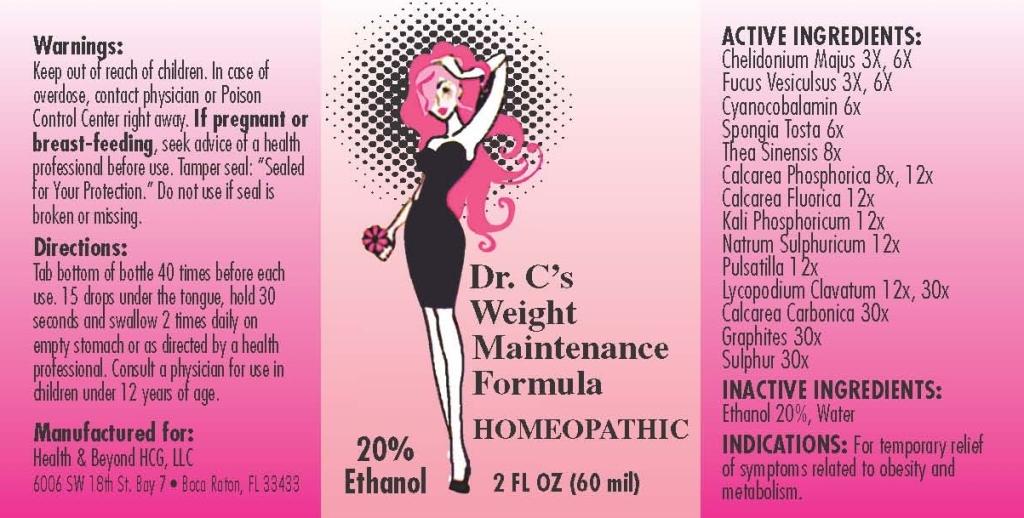 DRUG LABEL: Dr Cs Weight Maintenance
NDC: 57520-0639 | Form: LIQUID
Manufacturer: Apotheca Company
Category: homeopathic | Type: HUMAN OTC DRUG LABEL
Date: 20110715

ACTIVE INGREDIENTS: CHELIDONIUM MAJUS 6 [hp_X]/1 mL; FUCUS VESICULOSUS 6 [hp_X]/1 mL; CYANOCOBALAMIN 6 [hp_X]/1 mL; SPONGIA OFFICINALIS SKELETON, ROASTED 6 [hp_X]/1 mL; TEA LEAF OIL 8 [hp_X]/1 mL; TRIBASIC CALCIUM PHOSPHATE 12 [hp_X]/1 mL; CALCIUM FLUORIDE 12 [hp_X]/1 mL; POTASSIUM PHOSPHATE, DIBASIC 12 [hp_X]/1 mL; SODIUM SULFATE 12 [hp_X]/1 mL; PULSATILLA VULGARIS 12 [hp_X]/1 mL; LYCOPODIUM CLAVATUM SPORE 30 [hp_X]/1 mL; OYSTER SHELL CALCIUM CARBONATE, CRUDE 30 [hp_X]/1 mL; GRAPHITE 30 [hp_X]/1 mL; SULFUR 30 [hp_X]/1 mL
INACTIVE INGREDIENTS: WATER; ALCOHOL

Dr. C's Weight Maintenance

ACTIVE INGREDIENT

ACTIVE INGREDIENTS: Chelidonium majus 3X, 6X, Fucus vesiculosus 3X, 6X, Cyanocobalamin 6X, Spongia tosta 6X, Thea sinensis 8X, Calcarea phosphorica 8X, 12X, Calcarea fluorica 12X, Kali phosphoricum 12X, Natrum sulphuricum 12X, Pulsatilla 12X, Lycoodium clavatum 12X, 30X, Calcarea carbonica 30X, Graphites 30X, Sulphur 30X.

PURPOSE

INDICATIONS: For temporary relief of symptoms related to obesity and metabolism.

WARNINGS

WARNINGS: Keep out of reach of children. In case of overdose, contact physician or Poison Control Center right away.

If pregnant or breast-feeding, seek advice of a health professional before use.

Tamper seal: "Sealed for Your Protection." Do not use if seal is broken or missing.

DOSAGE AND ADMINISTRATION

DIRECTIONS: Tap bottom of bottle 40 times before each use. 15 drops under the tongue, hold 30 seconds and swallow. Take 2 times daily on empty stomach or as directed by a health professional. Consult a physician for use in children under 12 years of age.

INACTIVE INGREDIENTS: Ethanol 20%, Water.

KEEP OUT OF REACH OF CHILDREN. In case of overdose, contact physician or Poison Control Center right away.

INDICATIONS AND USAGE

INDICATIONS: For temporary relief of symptoms related to obesity and metabolism.

QUESTIONS

Manufactured for:

Health and Beyond HCG, LLC

6006 SW 18th St. Bay 7

Boca Raton, FL 33433

PACKAGE LABEL

Dr Cs Weight Maintenance Formula

HOMEOPATHIC

2 FL OZ (60 ml)